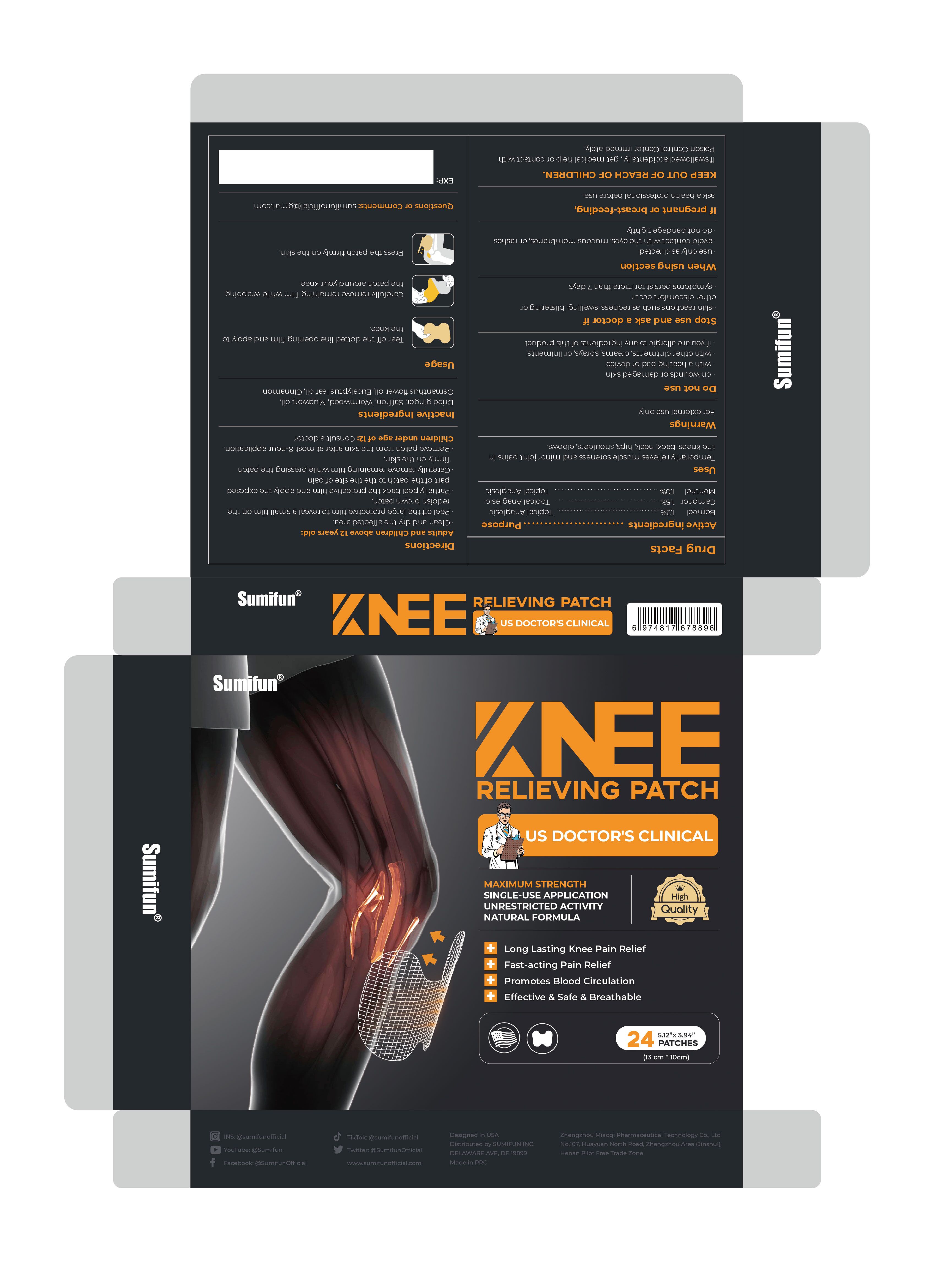 DRUG LABEL: Sumifun Knee Relieving Patch
NDC: 83781-008 | Form: PATCH
Manufacturer: Zhengzhou Miaoqi Pharmaceutical Technology Co., Ltd
Category: otc | Type: HUMAN OTC DRUG LABEL
Date: 20240106

ACTIVE INGREDIENTS: CAMPHOR (SYNTHETIC) 1.5 g/100 1; BORNEOL 1.2 g/100 1; MENTHOL 1 g/100 1
INACTIVE INGREDIENTS: SAFFRON; ARTEMISIA VULGARIS TOP OIL; WORMWOOD; EUCALYPTUS OIL; CINNAMON; GINGER; OSMANTHUS FRAGRANS FLOWER

83781-008

Active Ingredient

Borneol 1.2%
Camphor 1.5%
Menthol 1.0%

Purpose

Topical Anaglesic

Use

Temporarily relieves muscle soreness and minor joint pains in the knees, back,neck,hips,shoulders,elbows.

Warnings

For external use only.

Do not use

·on wounds or damaged skin
·with a heating pad or device
·with other ointments, creams, sprays, or liniments
·if you are allergic to any ingredients of this product

When Using

·use only as directed
·avoid contact with the eyes, mucous membranes, or rashes
·do not bandage tightly

Stop Use

·skin reactions such as redness,swelling,blistering or other discomfort occur
·symptoms persist for more than 7 days

Ask Doctor

Children under age of 12

Keep Out Of Reach Of Children

Directions

·Clean and dry the affected area.
·Peel off the large protective film to reveal a small film on the reddish brown patch.
·Partially peel back the protective film and apply the exposed part of the patch to the the site of pain.
·Carefully remove remaining film while pressing the patch firmly on the skin.
·Remove patch from the skin after at most 8-hour application.

Inactive ingredients

Dried ginger, Saffron, Wormwood, Mugwort oil, Osmanthus flower oil, Eucalyptus leaf oil,Cinnamon

Questions

sumifunofficial@gmail.com